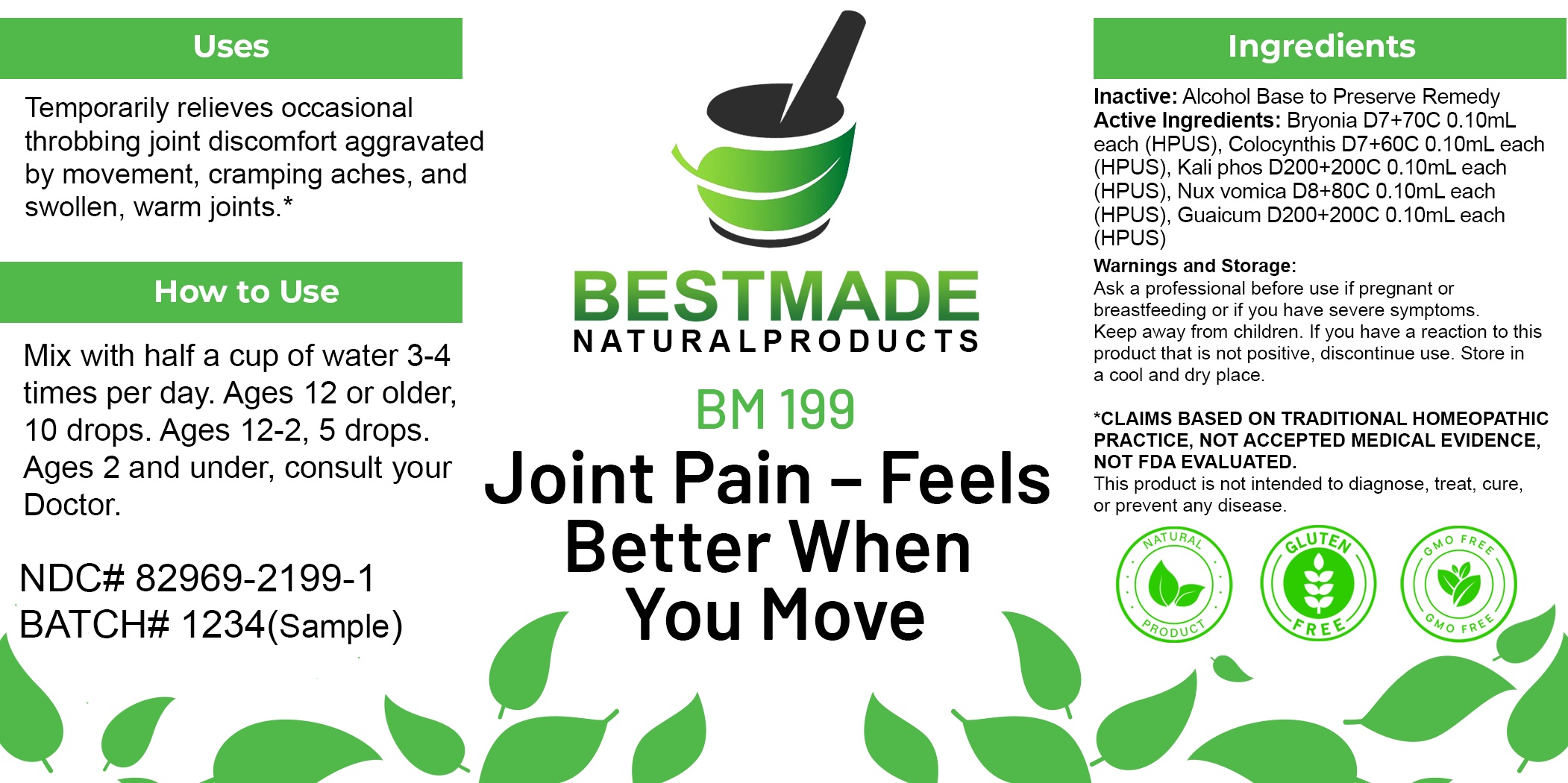 DRUG LABEL: Bestmade Natural Products BM199
NDC: 82969-2199 | Form: LIQUID
Manufacturer: Bestmade Natural Products
Category: homeopathic | Type: HUMAN OTC DRUG LABEL
Date: 20250225

ACTIVE INGREDIENTS: CITRULLUS COLOCYNTHIS FRUIT PULP 30 [hp_C]/30 [hp_C]; BRYONIA ALBA ROOT 30 [hp_C]/30 [hp_C]; STRYCHNOS NUX-VOMICA SEED 30 [hp_C]/30 [hp_C]; GUAIACUM OFFICINALE RESIN 30 [hp_C]/30 [hp_C]; DIBASIC POTASSIUM PHOSPHATE 30 [hp_C]/30 [hp_C]
INACTIVE INGREDIENTS: ALCOHOL 30 [hp_C]/30 [hp_C]

BM199

DOSAGE AND ADMINISTRATION

How to Use

Mix with half a cup of water 3-4 times per day. Ages 12 or older, 10 drops. Ages 12-2, 5 drops. Ages 2 and under, consult your Doctor.

Inactive:

Alcohol Base to Preserve Product

ACTIVE INGREDIENTS

Bryonia D7+70C 0.10mL each (HPUS), Colocynthis D7+60C 0.10mL each (HPUS), Kali phos D200+200C 0.10mL each (HPUS), Nux vomica D8+80C 0.10mL each (HPUS), Guaicum D200+200C 0.10mL each (HPUS)

KEEP OUT OF REACH OF CHILDREN

Warnings and Storage:

Ask a professional before use if pregnant or breastfeeding or if you have severe symptoms.

Keep away from children. If you have a reaction to this product that is not positive, discontinue use. Store in a cool and dry place

*CLAIMS BASED ON TRADITIONAL HOMEOPATHIC PRACTICE, NOT ACCEPTED MEDICAL EVIDENCE NOT FDA EVALUATED.
This product is not intended to diagnose, treat, cure, or prevent any disease.

Warnings and Storage:

Ask a professional before use if pregnant or breastfeeding or if you have severe symptoms.

Keep away from children. If you have a reaction to this product that is not positive, discontinue use. Store in a cool and dry place

*CLAIMS BASED ON TRADITIONAL HOMEOPATHIC PRACTICE, NOT ACCEPTED MEDICAL EVIDENCE NOT FDA EVALUATED.
This product is not intended to diagnose, treat, cure, or prevent any disease.

Uses
Temporarily relieves occasional throbbing joint discomfort aggravated by movement, cramping aches, and swollen, warm joints.*

Uses
Temporarily relieves occasional throbbing joint discomfort aggravated by movement, cramping aches, and swollen, warm joints.*

Entire package label